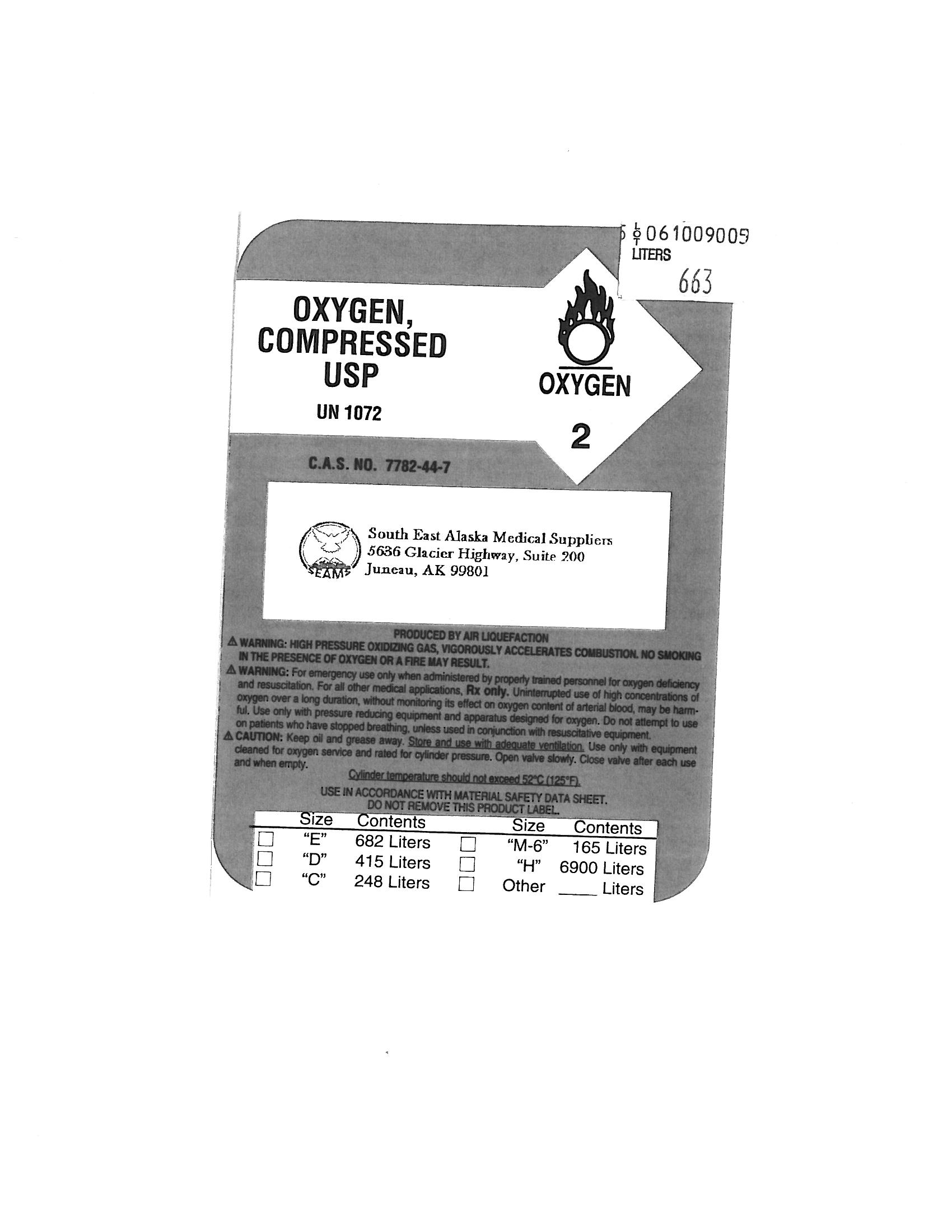 DRUG LABEL: OXYGEN
NDC: 61680-0622 | Form: GAS
Manufacturer: South East Alaska Medical Suppliers Inc. 
Category: prescription | Type: HUMAN PRESCRIPTION DRUG LABEL
Date: 20090831

ACTIVE INGREDIENTS: OXYGEN 99 L/100 L

OXYGEN